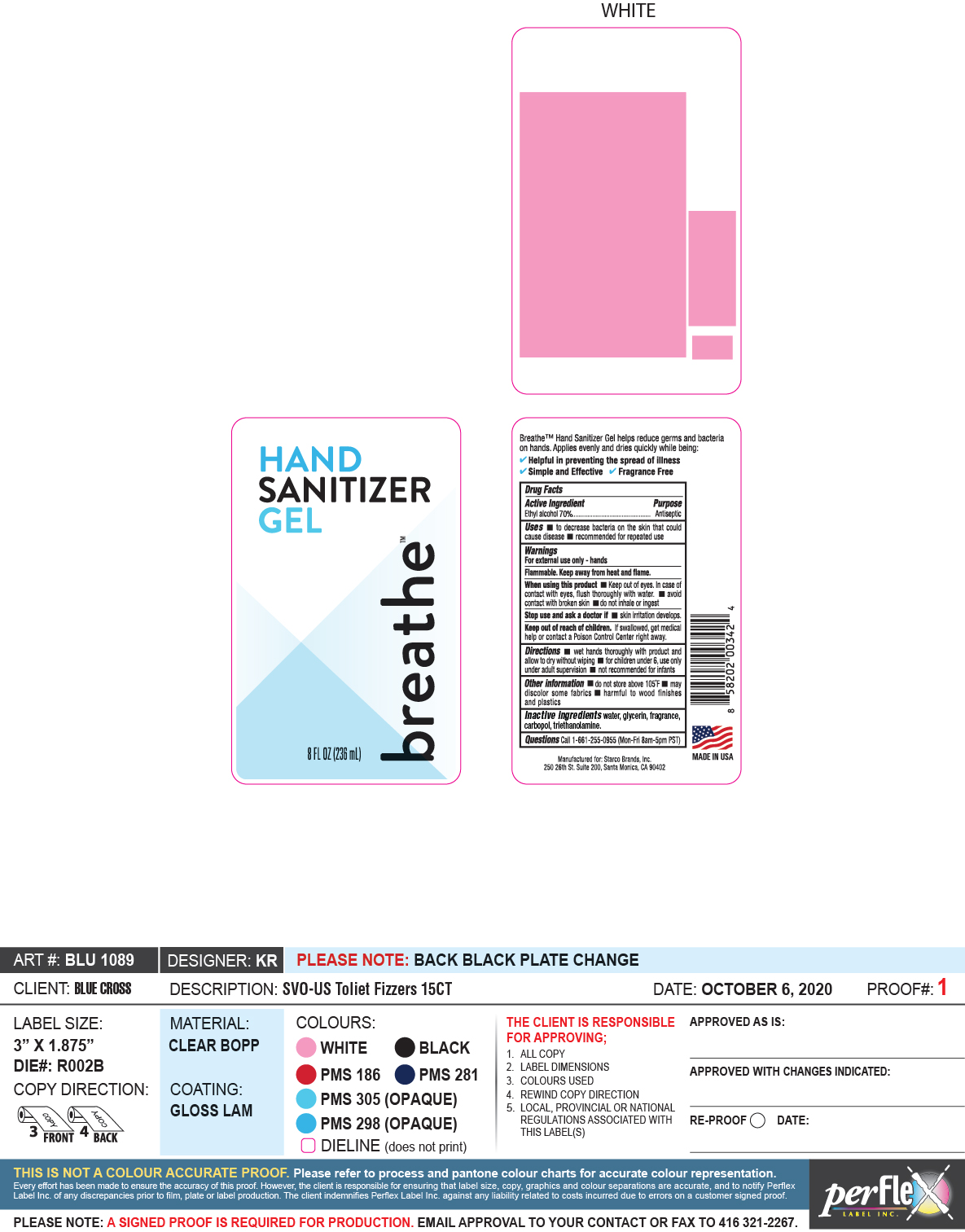 DRUG LABEL: Breathe Hand Sanitizer Gel
NDC: 22431-010 | Form: GEL
Manufacturer: Blue Cross Laboratories, Inc.
Category: otc | Type: HUMAN OTC DRUG LABEL
Date: 20201006

ACTIVE INGREDIENTS: ALCOHOL 70 mL/100 mL
INACTIVE INGREDIENTS: GLYCERIN; CARBOMER HOMOPOLYMER, UNSPECIFIED TYPE; WATER; TROLAMINE

Breathe Hand Sanitizer Gel

Active Ingredient(s)

Ethyl alcohol 70% Purpose: Antiseptic

Purpose

Antiseptic

Use

- to decrease bacteria on the skin that could cause disease.
- recommended for repeated use

Warnings

For external use only- hands

Flammable. Keep away from heat or flame

When using this product keep out of eyes. In case of contact with eyes, flush thoroughly with water.

avoid contact with broken skin. do not inhale or ingest.

Stop use and ask a doctor if irritation develops

Keep out of reach of children. If swallowed, get medical help or contact a Poison Control Center right away.

Directions

- wet hands thoroughly with product and allow to dry without wiping.
- for children under 6 use only under supervision
- not recommended for infants

Other information

- do not store above 105 F
- may discolor some fabrics
- harmful to wood finishes and plastics

Inactive ingredients

water, glycerin, fragrance, carbopol, triethanolamine

Package Label - Principal Display Panel

breathe Hand Sanitizer Gel

8 FL OZ (236 mL)